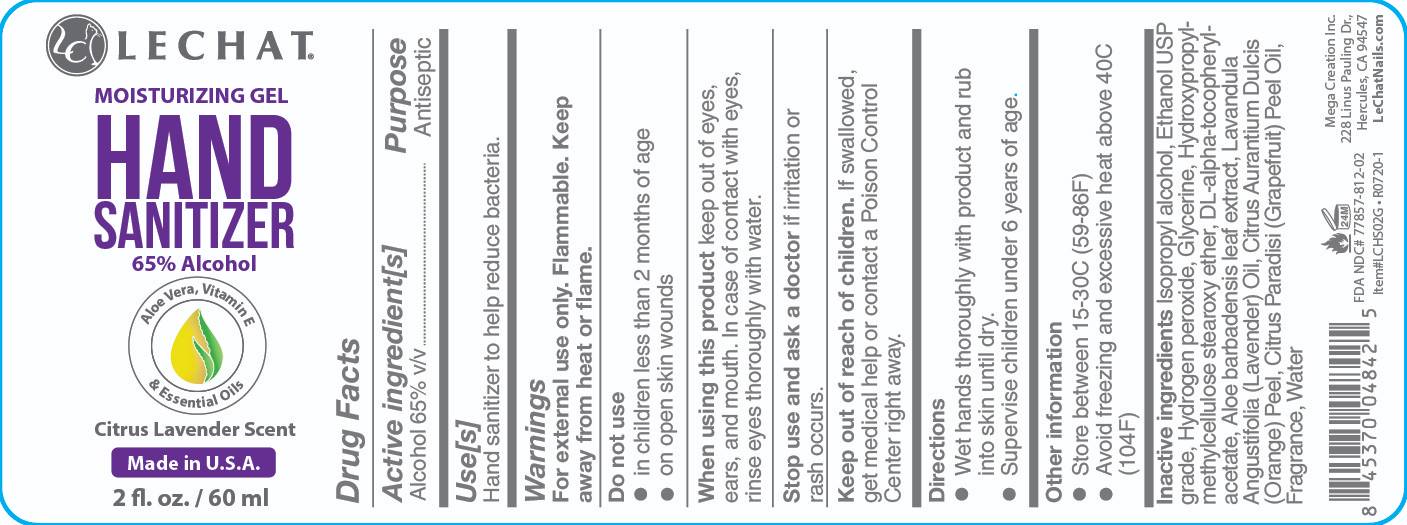 DRUG LABEL: LECHAT
NDC: 77857-812 | Form: GEL
Manufacturer: Mega Creation Inc.
Category: otc | Type: HUMAN OTC DRUG LABEL
Date: 20221024

ACTIVE INGREDIENTS: ALCOHOL 65 mL/100 mL
INACTIVE INGREDIENTS: GLYCERIN; HYDROGEN PEROXIDE; WATER; ALOE VERA LEAF; HYPROMELLOSES; CITRUS PARADISI FRUIT OIL; LAVENDER OIL; ORANGE PEEL; FRAGRANCE GREEN APPLE ORC2001072; .ALPHA.-TOCOPHEROL ACETATE, DL-; ISOPROPYL ALCOHOL

LECHAT Sanitizer Gel

Active Ingredient(s)

Ethyl Alcohol 65% v/v. Purpose: Antiseptic

Purpose

Antiseptic, Hand Sanitizer

Use

Hand Sanitizer to help reduce bacteria.

Warnings

For external use only.

Flammable.

Keep away from heat or flame

Do not use

- in children less than 2 months of age
- on open skin wounds

When using this product keep out of eyes, ears, and mouth. In case of contact with eyes, rinse eyes thoroughly with water.
Stop use and ask a doctor if irritation or rash occurs. These may be signs of a serious condition.
Keep out of reach of children. If swallowed, get medical help or contact a Poison Control Center right away.

Stop use and ask a doctor if irritation or rash occurs. These may be signs of a serious condition.

Keep out of reach of children. If swallowed, get medical help or contact a Poison Control Center right away.

Directions

- Wet hands thoroughly with the product and rub it on the skin untill dry.
- Supervise children under 6 years of age when using this product to avoid swallowing.

Other information

- Store between 15-30 C (59-86F)
- Avoid freezing & excessive heat above 40C (104F)

Inactive ingredients

glycerin, hydrogen peroxide, purified water, isopropyl alcohol, hydroxypropyl methylcellulose, dl alpha-tocopheryl acetate, Aloe barbadensis leaf extract, Lavandula Angustifolia oil, citrus Aurantium Dulcis peel, citrus paradisi peel oil, Fragrance

Package Label - Principal Display Panel

60mL NDC: 77857-812-02